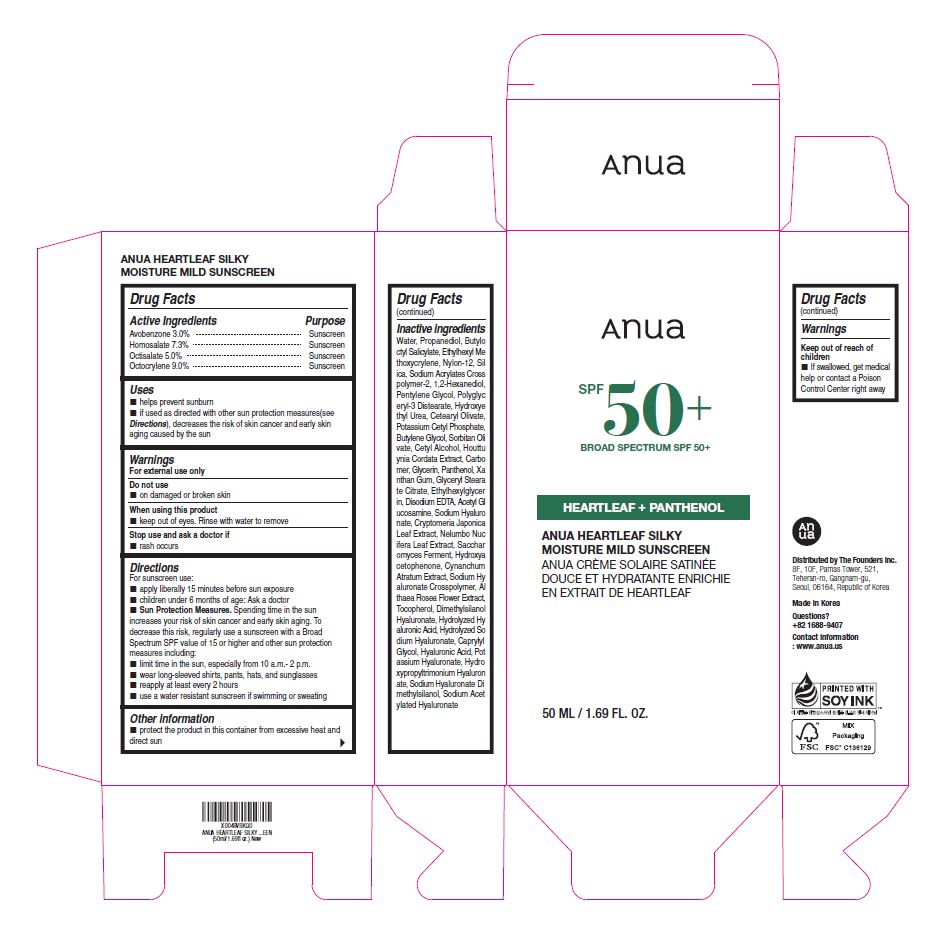 DRUG LABEL: ANUA HEARTLEAF SILKY MOISTURE MILD SUNSCREEN
NDC: 84610-100 | Form: CREAM
Manufacturer: The Founders Inc.
Category: otc | Type: HUMAN OTC DRUG LABEL
Date: 20240919

ACTIVE INGREDIENTS: OCTOCRYLENE 90 mg/1 mL; HOMOSALATE 73 mg/1 mL; OCTISALATE 50 mg/1 mL; AVOBENZONE 30 mg/1 mL
INACTIVE INGREDIENTS: BUTYLOCTYL SALICYLATE; NYLON-12; SILICON DIOXIDE; CETEARYL OLIVATE; SODIUM ACRYLATES CROSSPOLYMER-2; SORBITAN OLIVATE; WATER; XANTHAN GUM; PENTYLENE GLYCOL; CARBOMER 940; DIMETHYLSILANOL HYALURONATE; POTASSIUM CETYL PHOSPHATE; HYDROXYACETOPHENONE; HYALURONIC ACID; 1,2-HEXANEDIOL; HYDROXYETHYL UREA; GLYCERIN; N-ACETYLGLUCOSAMINE; PROPANEDIOL; ETHYLHEXYL METHOXYCRYLENE; PANTHENOL; CETYL ALCOHOL; ETHYLHEXYLGLYCERIN; EDETATE DISODIUM; CRYPTOMERIA JAPONICA LEAF; NELUMBO NUCIFERA LEAF; ALCEA ROSEA FLOWER; GLYCERYL STEARATE CITRATE; CAPRYLYL GLYCOL; SODIUM ACETYLATED HYALURONATE; POLYGLYCERYL-3 DISTEARATE; HOUTTUYNIA CORDATA FLOWERING TOP; HYALURONATE SODIUM; BUTYLENE GLYCOL; TOCOPHEROL; POLYACRYLIC ACID (450000 MW)

ANUA HEARTLEAF SILKY MOISTURE MILD SUNSCREEN BROAD SPECTRUM SPF 50+

Drug Facts

Active Ingredients

Avobenzone 3.0%

Homosalate 7.3%

Octisalate 5.0%

Octocrylene 9.0%

Purpose

Sunscreen

Uses

■ helps prevent sunburn
■ if used as directed with other sun protection measures(see Directions), decreases the risk of skin cancer and early skin aging caused by the sun.

Warnings

For external use only

Do not use

■ on damaged or broken skin

When using this product

■ keep out of eyes. Rinse with water to remove

Stop Use and ask a doctor if

■ rash occurs

Keep out of reach of children.

If product is swallowed, get medical help or contact a Poison Control Center right away.

Directions

For sunscreen use:

■ apply liberally 15 minutes before sun exposure

■ children under 6 months of age: Ask a doctor

■ Sun Protection Measures. Spending time in the sun increases your risk of skin cancer and early skin aging. To decrease this risk, regularly use a sunscreen with a Broad Spectrum SPF value of 15 or higher and other sun protection measures including:

■ limit time in the sun, especially from 10 a.m.- 2 p.m.

■ wear long-sleeved shirts, pants, hats, and sunglasses

■ reapply at least every 2 hours

■ use a water resistant sunscreen if swimming or sweating

Other Information

■ Protect the product in this container from excessive heat and direct sun

Inactive ingredients

Water, Propanediol, Butyloctyl Salicylate, Ethylhexyl Methoxycrylene, Nylon-12, Silica, Sodium Acrylates Crosspolymer-2, 1,2-Hexanediol, Pentylene Glycol, Polyglyceryl-3 Distearate, Hydroxyethyl Urea, Cetearyl Olivate, Potassium Cetyl Phosphate, Butylene Glycol, Sorbitan Olivate, Cetyl Alcohol, Houttuynia Cordata Extract, Carbomer, Glycerin, Panthenol, Xanthan Gum, Glyceryl Stearate Citrate, Ethylhexylglycerin, Disodium EDTA, Acetyl Glucosamine, Sodium Hyaluronate, Cryptomeria Japonica Leaf Extract, Nelumbo Nucifera Leaf Extract, Saccharomyces Ferment, Hydroxyacetophenone, Cynanchum Atratum Extract, Sodium Hyaluronate Crosspolymer, Althaea Rosea Flower Extract, Tocopherol, Dimethylsilanol Hyaluronate, Hydrolyzed Hyaluronic Acid, Hydrolyzed Sodium Hyaluronate, Caprylyl Glycol, Hyaluronic Acid, Potassium Hyaluronate, Hydroxypropyltrimonium Hyaluronate, Sodium Hyaluronate Dimethylsilanol, Sodium Acetylated Hyaluronate

Questions ?

+82 1688-9407

Contact information

: www.anua.us